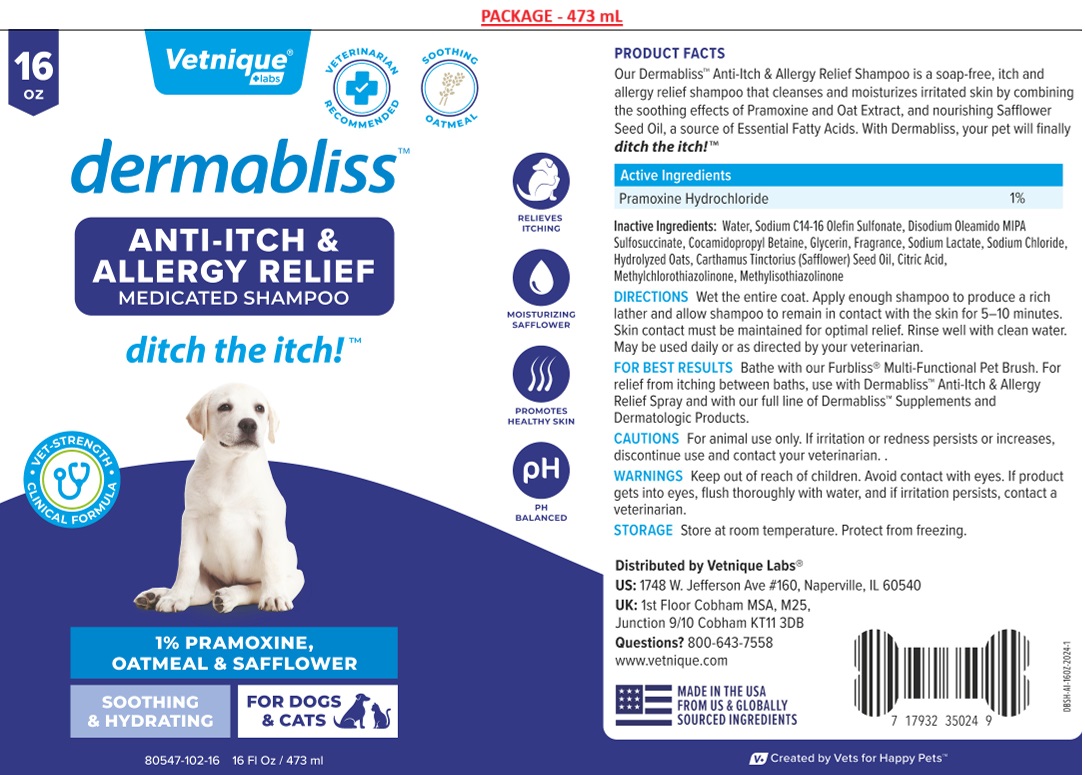 DRUG LABEL: dermabliss ANTI-ITCH and ALLERGY RELIEF
NDC: 80547-102 | Form: SHAMPOO
Manufacturer: Vetnique Labs Llc
Category: animal | Type: OTC ANIMAL DRUG LABEL
Date: 20241026

ACTIVE INGREDIENTS: PRAMOXINE HYDROCHLORIDE 10 mg/1 mL
INACTIVE INGREDIENTS: WATER; SODIUM C14-16 OLEFIN SULFONATE; DISODIUM OLEAMIDO MIPA-SULFOSUCCINATE; COCAMIDOPROPYL BETAINE; GLYCERIN; SODIUM LACTATE; SODIUM CHLORIDE; OAT; SAFFLOWER OIL; CITRIC ACID MONOHYDRATE; METHYLCHLOROISOTHIAZOLINONE; METHYLISOTHIAZOLINONE

dermabliss™ ANTI-ITCH & ALLERGY RELIEF MEDICATED SHAMPOO

Active Ingredients

Pramoxine Hydrochloride 1%

PURPOSE

ANTI-ITCH & ALLERGY RELIEF

INDICATIONS AND USAGE

PRODUCT FACTS

Our Dermabliss™ Anti-Itch & Allergy Relief Shampoo is a soap-free, itch and allergy relief shampoo that cleanses and moisturizes irritated skin by combining the soothing effects of Pramoxine and Oat Extract, and nourishing Safflower Seed Oil, a source of Essential Fatty Acids. With Dermabliss, your pet will finally ditch the itch!™

DOSAGE AND ADMINISTRATION

DIRECTIONS Wet the entire coat. Apply enough shampoo to produce a rich lather and allow shampoo to remain in contact with the skin for 5-10 minutes. Skin contact must be maintained for optimal relief. Rinse well with clean water. May be used daily or as directed by your veterinarian.

FOR BEST RESULTS Bathe with our Furbliss® Multi-Functional Pet Brush. For relief from itching between baths, use with Dermabliss™ Anti-Itch & Allergy Relief Spray and with our full line of Dermabliss™ supplements and Dermatologic products.

PRECAUTIONS

CAUTIONS For animal use only. If irritation or redness persists or increases, discontinue use and contact your veterinarian.

WARNINGS

WARNING Keep out of reach of children. Avoid contact with eyes. If product gets into eyes, flush thoroughly with water, and if irritation persists, contact a veterinarian.

STORAGE Store at room temperature. Protect from freezing.

INACTIVE INGREDIENT

Ingredients: Water, Sodium C14-16 Olefin Sulfonate, Disodium Oleamido MIPA Sulfosuccinate, Cocamidopropyl Betaine, Glycerin, Fragrance, Sodium Lactate, Sodium Chloride, Hydrolyzed Oats, Carthamus Tinctorius (Safflower) Seed Oil, Citric Acid, Methylchloroisothiazolinone, Methylisothiazolinone

VETERINARIAN RECOMMENDED

SOOTHING OATMEAL

ditch the itch! ™

• VET-STRENGTH • CLINICAL FORMULA

SOOTHING & HYDRATING

FOR DOGS & CATS

RELIEVES ITCHING

MOISTURIZING SAFFLOWER

PROMOTES HEALTHY SKIN

PH BALANCED

Distributed by Vetnique Labs®US: 1748 W. Jefferson Ave #160, Naperville, IL 60540
UK: 1st Floor Cobham MSA, M25,
Junction 9/10 Cobham KT11 3DB

Questions? 800-643-755
www.vetnique.com

MADE IN THE USA
FROM US & GLOBALLY SOURCED INGREDIENTS

V+ Created by Vets for Happy Pets™